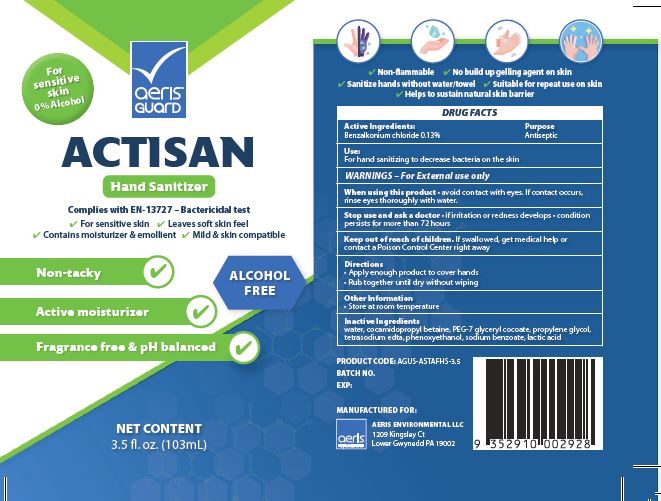 DRUG LABEL: AerisGuard Actisan Hand Sanitizer
NDC: 81124-001 | Form: SOLUTION
Manufacturer: Aeris Environmental LLC
Category: otc | Type: HUMAN OTC DRUG LABEL
Date: 20221212

ACTIVE INGREDIENTS: BENZALKONIUM CHLORIDE 0.13 g/100 mL
INACTIVE INGREDIENTS: LACTIC ACID; EDETATE SODIUM; PEG-7 GLYCERYL COCOATE; SODIUM BENZOATE; PHENOXYETHANOL; WATER; COCAMIDOPROPYL BETAINE; PROPYLENE GLYCOL

Active Ingredients

Benzalkonium chloride 0.13%

Purpose

Antiseptic

Uses

For hand sanitizing to decrease bacteria on the skin

WARNINGS

For External use only

When using this product avoid contact with eyes.

If contact occurs, rinse eyes thoroughly with water.

Stop use and ask a doctor

- if irritation or redness develops
- condition persists for more than 72 hours

Keep out of reach of children.

If swallowed, get medical help or contact a Poison Control Center right away

Directions

- Apply enough product to cover hands
- Rub together until dry without wiping

Other Information

Store at room temperature

Inactive Ingredients

water, cocamidopropyl betaine, PEG-7 glyceryl cocoate, propylene glycol, tetrasodium edta, phenoxyethanol, sodium benzoate, lactic acid

PACKAGE LABEL

For

sensitive

skin

0% Alcohol

aeris

guard

ACTISAN

Hand Sanitizer

Complies with EN-13727-Bactericidal test

For sensitive skin Leaves soft skin feel

Contains moisturizer and emollient Mild and skin compatible

Non-tacky

Active moisturizer

Fragrance free and pH balanced

ALCOHOL

FREE

NET CONTENTS

3.5 fl. oz. (103mL)